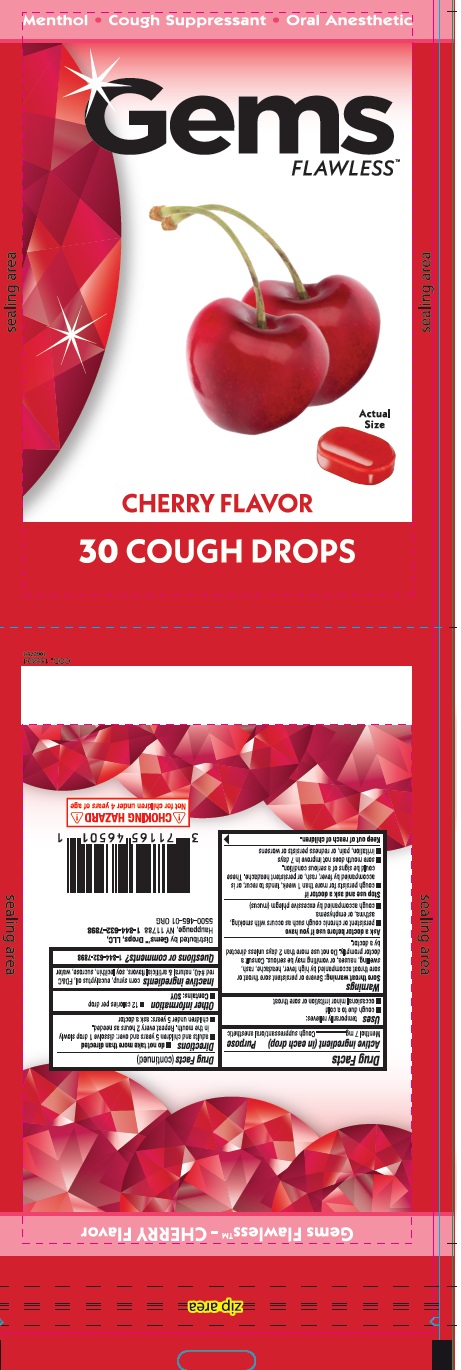 DRUG LABEL: Cough Drops Gems Flawless Cherry Flavor 30ct
NDC: 71165-032 | Form: LOZENGE
Manufacturer: Riclan S.A.
Category: otc | Type: HUMAN OTC DRUG LABEL
Date: 20251118

ACTIVE INGREDIENTS: LEVOMENTHOL 7 mg/1 1
INACTIVE INGREDIENTS: SUCROSE; CORN SYRUP; EUCALYPTOL; LECITHIN, SOYBEAN; FD&C RED NO. 40

Active Ingredient

Menthol

Purpose

Cough Suppressant / Oral anesthetic

Use

Temporarily relieves:

- cough as may occur with a cold
- occasional minor irritation and sore throat

Warnings

Sore throat warning: Severe or persistent sore throat or sore throat accompanied by high fever, headache, rash, swelling, nausea, or vomiting may be serious. Consult a doctor Promptly. Do not use more than 2 days unless directed by a doctor.

Ask a doctor before use if you have :

- persistent or chronic cough such as occurs with smoking, asthma, or emphysema
- cough accompanined by excessive phlegm (mucus)

stop use and ask doctor if

- cough persists for more than 1 week , tends to recur, or is accompanied by fever, rash, or persistent headache. These could be signs of a serious condition.
- sore throat is severe, or irritation, pain or redness lasts or worsens
- sore mouth does not improve in 7 days

Directions

- do not take more than directed
- adults and children 5 years and over : dissolve 1 drop slowly in the mouth. Repeate every 2 hours as needed.
- children under 5 years : ask a doctor

Other information

- 12 calories per drop
- Contains : Soy

Inactive ingredients

corn syrup, eucalyptus oil, natural & artificial flavors, soy lecithin, sucrose and water, FD & C red #40